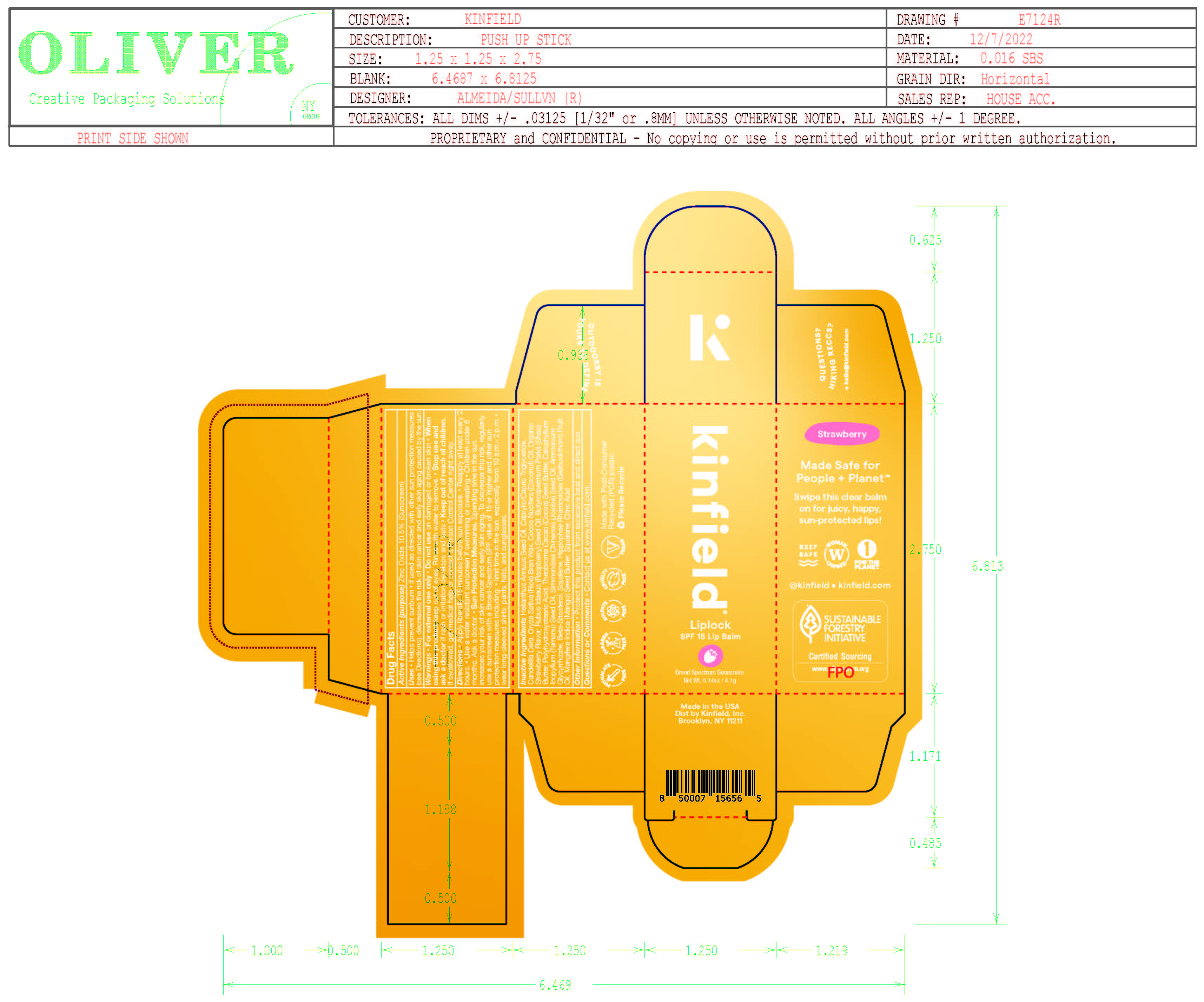 DRUG LABEL: Kinfield Liplock SPF 15 Lip Balm Broad Spectrum Sunscreen
NDC: 81750-100 | Form: STICK
Manufacturer: Kinfield, Inc.
Category: otc | Type: HUMAN OTC DRUG LABEL
Date: 20251230

ACTIVE INGREDIENTS: ZINC OXIDE 10.5 g/100 g
INACTIVE INGREDIENTS: HELIANTHUS ANNUUS WHOLE; CANDELILLA WAX; ORYZA SATIVA WHOLE; COCOS NUCIFERA WHOLE; RASPBERRY SEED OIL; SHEA BUTTER; POLYHYDROXYSTEARIC ACID (2300 MW); THEOBROMA CACAO WHOLE; CALOPHYLLUM INOPHYLLUM WHOLE; SIMMONDSIA CHINENSIS SEED; AMMONIUM GLYCYRRHIZATE; .BETA.-SITOSTEROL; SQUALENE; HIPPOPHAE RHAMNOIDES FRUIT OIL; MANGIFERA INDICA SEED BUTTER; SQUALANE; CITRIC ACID ACETATE

DRUG FACTS

Active Ingredients

Zinc Oxide 10.5%

Uses

• helps prevent sunburn • if used as directed with other
sun protection measures (see Directions), decreases the
risk of skin cancer and early skin aging caused by the sun

Warnings

For external use only
Do not use on damaged or broken skin.
When using this product keep out of eyes. Rinse with water to remove.
Stop use and ask a docor if rash occurs
Keep out of reach of children. If swalled, get medical help or contact a Poison Control Center right away.

Directions

• apply generously 15 minutes before sun exposure
• reapply: •at least every 2 hours.

• use a water resistant sunscreen if swimming or sweating
• Sun Protection Measures. Spending time in the sun

increases your risk of skin cancer and early skin aging. To decrease
this risk, regularly use a sunscreen with a Broad Spectrum SPF
value of 15 or higher and other sun protection measures including:
• limit time in the sun, especially from 10 a.m. - 2 p.m.
• wear long-sleeved shirts, pants, hats, and sunglasses
• children under 6 months of age: Ask a doctor

Inactive ingredients

Helianthus Annuus Seed Oil, Caprylic/Capric Triglyceride, Candelilla Cera, Oryza Sativa (Rice) Bran Wax, Cocos Nucifera (Coconut) Oil, Organic Strawberry Flavor, Rubus Idaeus (Raspberry) Seed Oil, Butyrospermum Parkii (Shea) Butter, Polyhydroxystearic Acid, Theobrama Cacao (Cocoa) Seed Butter, Calophyllum Inopyllum (Teamanu) Seed Oil, Simmondsia Chinensis (Jojoba) Seed Oil, Ammonium Glycyrrhizate, Beta-Sitosterol, Squalene, Hippophae Rhamnoides (Seabuckthorn) Fruti Oil, Mangifera Indica (Mango) Seed Butter, Squalane, Citric Acid

Other Information

• protect the product in this container from excessive
heat and direct sun

Questions or Comments?

Conctact us at www.kinfield.com

Purpose

Purpose: Sunscreen

Keep out of reach of children. If product is swallowed, get medical help or contact a Poison Control Center right away.